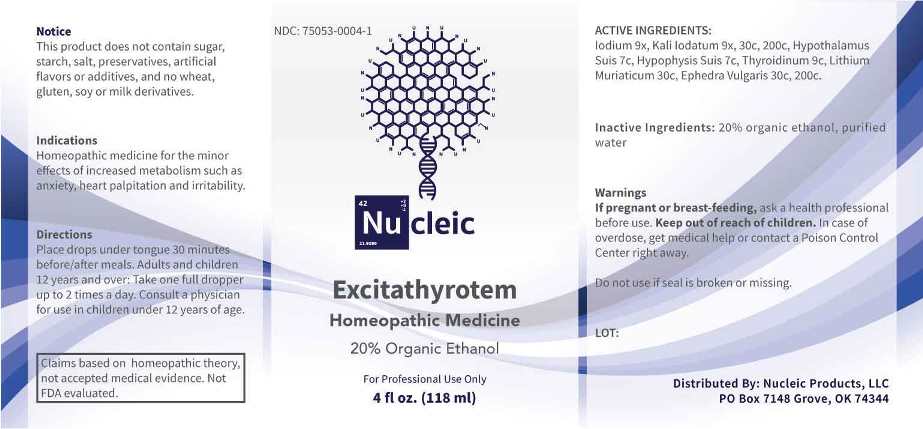 DRUG LABEL: Excitathyrotem
NDC: 75053-0004 | Form: LIQUID
Manufacturer: Nucleic Products, LLC
Category: homeopathic | Type: HUMAN OTC DRUG LABEL
Date: 20240122

ACTIVE INGREDIENTS: IODINE 9 [hp_X]/1 mL; POTASSIUM IODIDE 9 [hp_X]/1 mL; BOS TAURUS HYPOTHALAMUS 7 [hp_C]/1 mL; SUS SCROFA PITUITARY GLAND 7 [hp_C]/1 mL; THYROID, UNSPECIFIED 9 [hp_C]/1 mL; LITHIUM CHLORIDE 30 [hp_C]/1 mL; EPHEDRA DISTACHYA FLOWERING TWIG 30 [hp_C]/1 mL
INACTIVE INGREDIENTS: WATER; ALCOHOL

DRUG FACTS:

ACTIVE INGREDIENTS:

Iodium 9X, Kali Iodatum 9X, 30C, 200C, Hypothalamus Suis 7C, Hypophysis Suis 7C, Thyroidinum (Suis) 9C, Lithium Muriaticum 30C, Ephedra Vulgaris 30C, 200C.

INDICATIONS:

Homeopathic medicine for the minor effects of increased metabolism such as anxiety, heart palpitation and irritability.

Claims based on homeopathic theory, not accepted medical evidence. Not FDA evaluated.

WARNINGS:

If pregnant or breast-feeding, ask a health professional before use.

Keep out of reach of children. In case of overdose, get medical help or contact a Poison Control Center right away.

Do not use if seal is broken or missing.

This Product does not contain sugar, starch, salt, preservatives, artificial flavors or additives, and no wheat, gluten, soy or milk derivatives.

Keep out of reach of children. In case of overdose, get medical help or contact a Poison Control Center right away.

DIRECTIONS:

Place drops under tongue 30 minutes before/after meals. Adults and children 12 years and over: Take one full dropper up to 2 times a day. Consult a physician for use in children under 12 years of age.

INDICATIONS:

Homeopathic medicine for the minor effects of increased metabolism such as anxiety, heart palpitation and irritability.

Claims based on homeopathic theory, not accepted medical evidence. Not FDA evaluated.

INACTIVE INGREDIENTS:

20% organic ethanol, purified water

QUESTIONS:

Distributed By:
Nucleic Products, LLC

PO Box 7148 Grove, OK 74344

PACKAGE LABEL DISPLAY:

NDC: 75053-0004-1

Nu cleic

Excitathyrotem

Homeopathic Medicine

For Professional Use Only

4 fl oz. (118 ml)